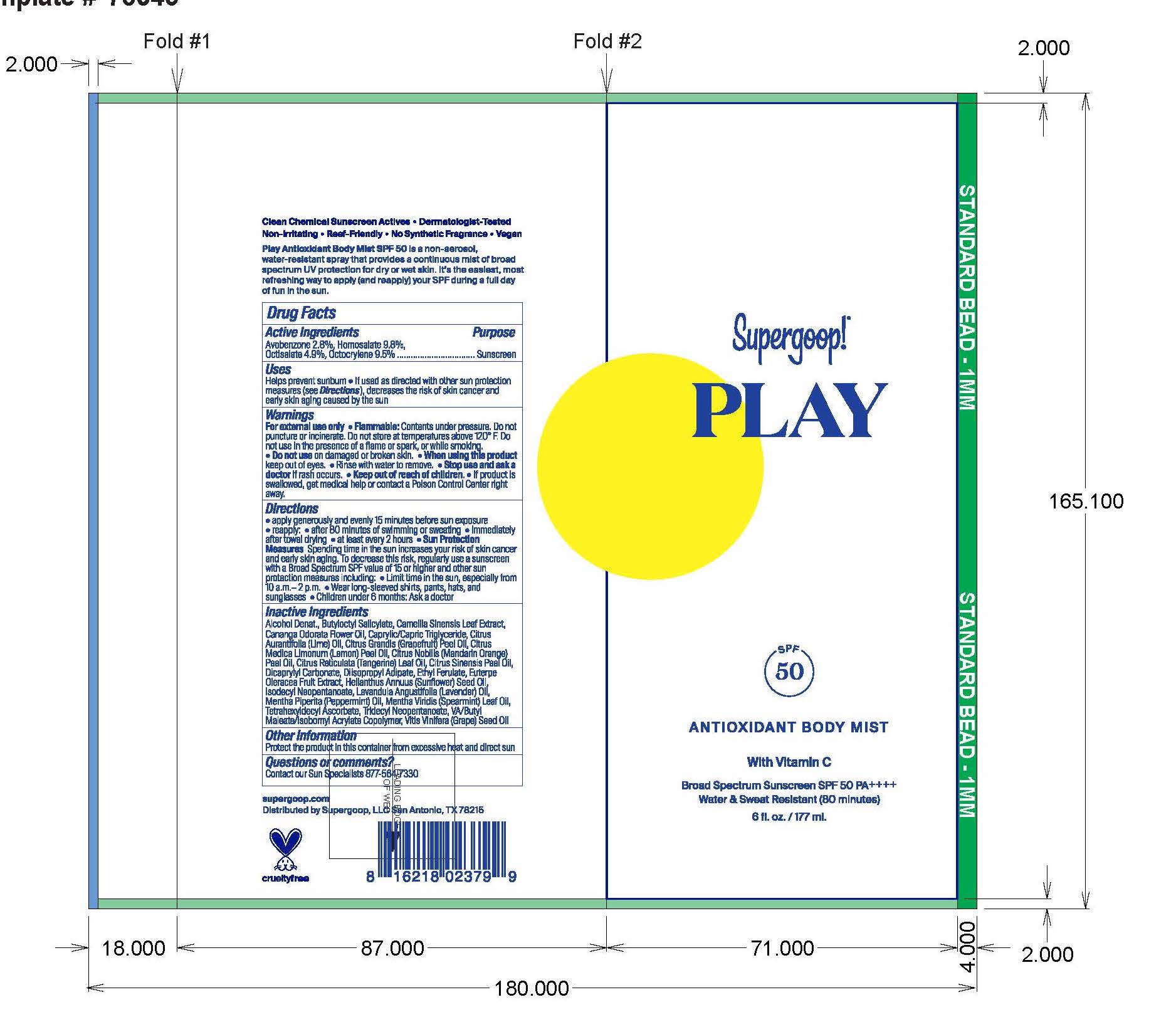 DRUG LABEL: PLAY Antioxidant Body Mist SPF 50 With Vitamin C
NDC: 75936-154 | Form: SPRAY
Manufacturer: Supergoop, LLC
Category: otc | Type: HUMAN OTC DRUG LABEL
Date: 20241204

ACTIVE INGREDIENTS: HOMOSALATE 9.8 g/100 mL; OCTISALATE 4.9 g/100 mL; OCTOCRYLENE 9.5 g/100 mL; AVOBENZONE 2.8 g/100 mL
INACTIVE INGREDIENTS: MEDIUM-CHAIN TRIGLYCERIDES; ORANGE OIL; ETHYL FERULATE; ACAI; ALCOHOL; BUTYLOCTYL SALICYLATE; GREEN TEA LEAF; CITRUS RETICULATA LEAF OIL; LAVENDER OIL; DICAPRYLYL CARBONATE; DIISOPROPYL ADIPATE; PEPPERMINT OIL; MENTHA SPICATA OIL; TETRAHEXYLDECYL ASCORBATE; GRAPE SEED OIL; LEMON OIL; MANDARIN OIL; CANANGA OIL; LIME OIL; SUNFLOWER OIL; ISODECYL NEOPENTANOATE; CITRUS MAXIMA FRUIT RIND OIL

PLAY Antioxidant Body Mist SPF 50 With Vitamin C

Active ingredients: Purpose

Avobenzene 3% Sunscreen

Homosalate 9.8% Sunscreen

Octisalate 4.9% Sunscreen

Octocrylene 9.5% Sunscreen

Uses
· helps prevent sunburn
· If used as directed with other sun protection measures (see Directions),
decreases the risk of skin cancer and early skin aging caused by the sun

Keep out of reach of children. If product is swallowed, get medical help or
contact a Poison Control Center right away.

Stop use and ask a doctor if rash occurs

WARNINGS

For external use only
Do not use on damaged or broken skin
When using this product keep out of eyes. Rinse with water to remove.

Directions
Apply generously and evenly 15 minutes before sun exposure
Reapply at least every 2 hours
Use a water resistant sunscreen if swimming or sweating
Sun Protection Measures. Spending time in the sun increases your risk of skin
cancer and early skin aging. To decrease this risk, regularly use a sunscreen
with broad spectrum SPF of 15 or higher and other sun protection measures
including:
· limit time in the sun, especially from 10 a.m. - 2 p.m.
· wear long-sleeve shirts, pants, hats, and sunglasses

Children under 6 months: Ask a doctor

INACTIVE INGREDIENT

Alcohol Denat., Butyloctyl Salicylate, Camellia Sinensis Leaf Extract, Cananga Odorata Flower Oil, Caprylic/Capric Triglyceride, Citrus Grandis (Grapfruit) Peel Oil, Citrus medica Limonium (Lemon) Oil, Citrus Nobilis (Mandarin Orange) Peel Oil, Citrus reticulata (Tangerine) Leaf Oil, Citrus Sinensis peel Oil, Dicaprylyl Carbonate, Diisopropyl adiipate, Ethyl Ferulate, Euterpe Oleracea Fruit Extract, Helianthuus Annuus (Sunflower) Seed Oil, Isodecyl Neopentanoate, Lavandula Angustifolia (Lavender) Oil, Mentha Piperita (Peppermint) Oil, Mentha Viridis(Spearmint) Tetrahexyldecyl Ascorbate, Tridecyl Neopentanoate, VA/Butyl Maleate/ Isobornyl Acrylate Copolymer, Vitis Vinifera (Grape) Seed Oil

PACKAGE LABEL

Supergoop! PLAY

SPF 50

ANTIOXIDANT BODY MIST

with Vitamin C

Broad Spectrum Sunscreen SPF 50

Water & Sweat Resistant (80 minutes)

6fl. oz./ 177 ml